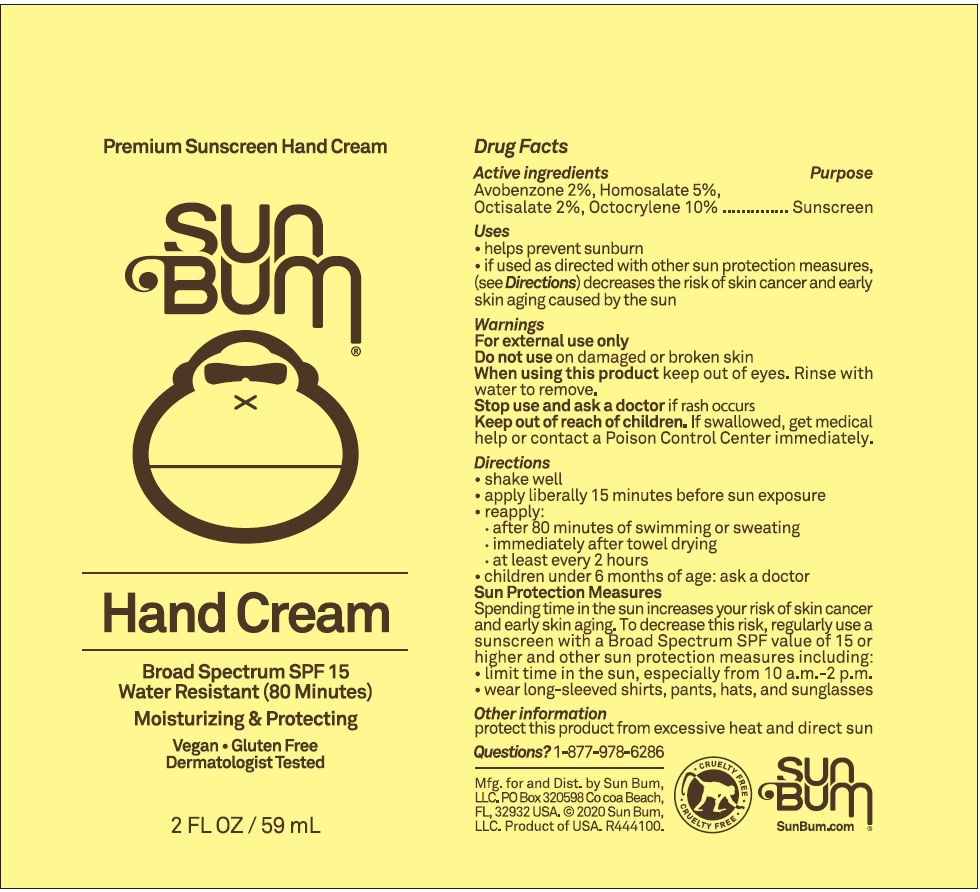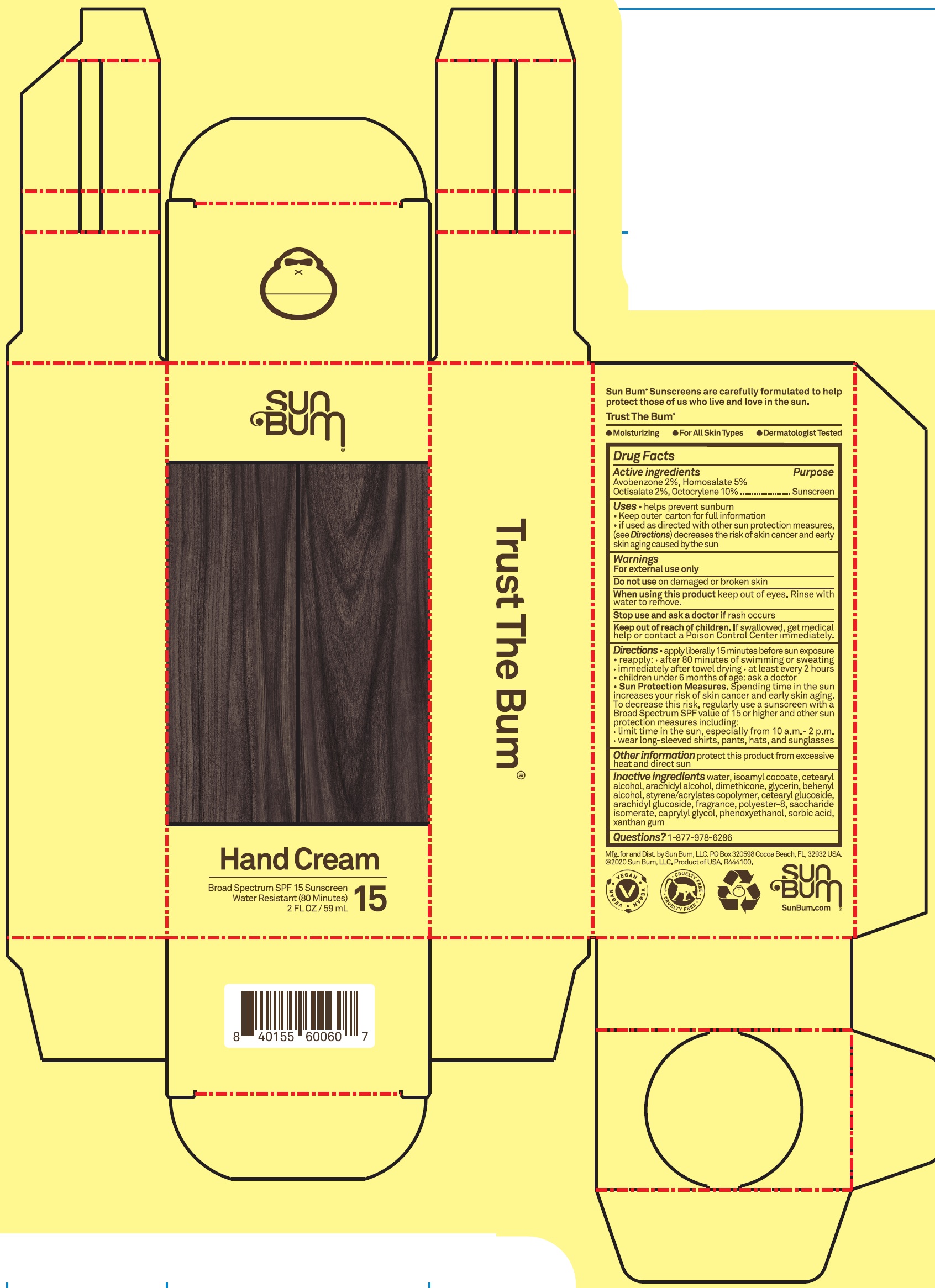 DRUG LABEL: Sun Bum Hand Cream SPF15
NDC: 69039-637 | Form: CREAM
Manufacturer: Sun Bum LLC
Category: otc | Type: HUMAN OTC DRUG LABEL
Date: 20220204

ACTIVE INGREDIENTS: AVOBENZONE 20 mg/1 mL; HOMOSALATE 50 mg/1 mL; OCTISALATE 20 mg/1 mL; OCTOCRYLENE 10 mg/1 mL
INACTIVE INGREDIENTS: WATER; ISOAMYL COCOATE; CETOSTEARYL ALCOHOL; ARACHIDYL ALCOHOL; DIMETHICONE; GLYCERIN; DOCOSANOL; STYRENE/ACRYLAMIDE COPOLYMER (500000 MW); CETEARYL GLUCOSIDE; ARACHIDYL GLUCOSIDE; PHENOXYETHANOL; SORBIC ACID; XANTHAN GUM

Sun Bum Hand Cream SPF15

Active ingredients

Avobenzone 2%,

Homosalate 5%,

Octisalate 2%,

Octocrylene 10%

Purpose

Sunscreen

Uses

- helps prevent sunburn
- Keep outer carton for full information
- if used as directed with other sun protection measures, (see Directions) decreases the risk of skin cancer and early skin aging caused by the sun

Warnings

For external use only

Do not use

on damaged or broken skin

When using this product

keep out of eyes. Rinse with water to remove.

Stop use and ask a doctor if

rash occurs

Keep out of reach of children.

If swallowed, get medical help or contact a Poison Control Center immediately.

Directions

- apply liberally 15 minutes before sun exposure
- reapply: • after 80 minutes of swimming or sweating • immediately after towel drying • at least every 2 hours
- children under 6 months of age: ask a doctor

Sun Protection Measures. Spending time in the sun increases your risk of skin cancer and early skin aging. To decrease this risk, regularly use a sunscreen with a Broad Spectrum SPF value of 15 or higher and other sun protection measures including:

- limit time in the sun, especially from 10 a.m.-2 p.m.
- wear long-sleeved shirts, pants, hats and sunglasses

Other information

protect this product from excessive heat and direct sun

Inactive ingredients

water, isoamyl cocoate, cetearyl alcohol, arachidyl alcohol, dimethicone, glycerin, behenyl alcohol, styrene/acrylates copolymer, cetearyl glucoside, arachidyl glucoside, fragrance, polyester-8, saccharide isomerate, aprylyl glycol, phenoxyethanol, sorbic acid, xanthan gum xanthan gum, phenoxyethanol, ethylhexylglycerin

Questions?

1-877-978-6286